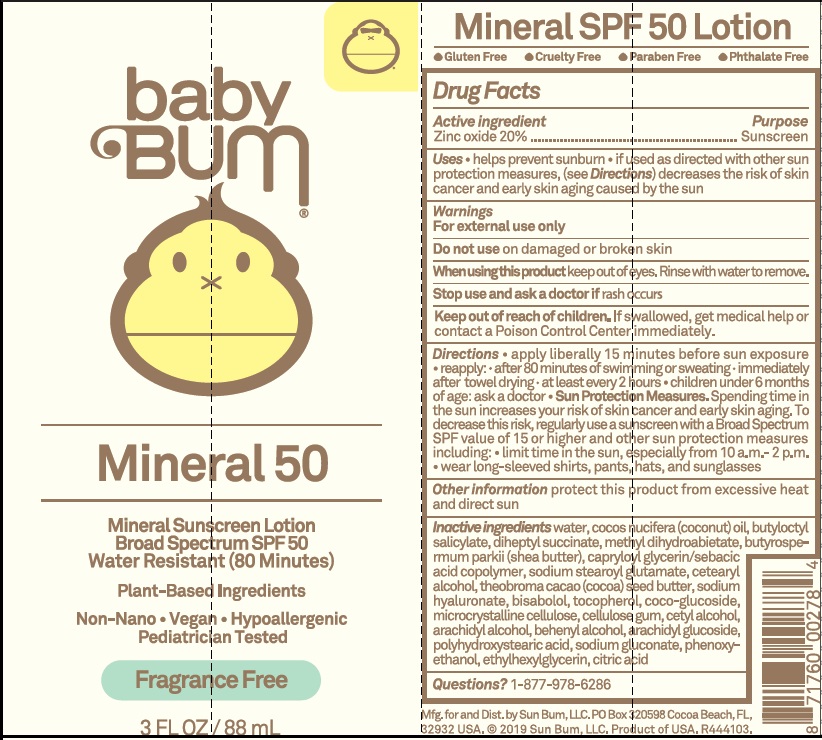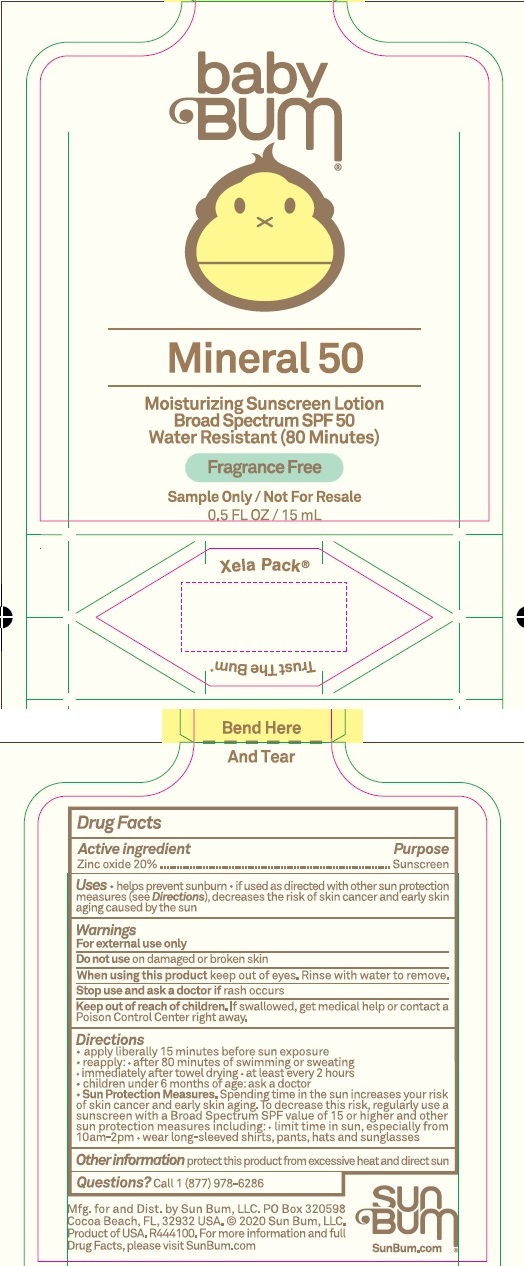 DRUG LABEL: Baby Bum SPF50 Mineral Sunscreen
NDC: 69039-255 | Form: CREAM
Manufacturer: Sun Bum, LLC
Category: otc | Type: HUMAN OTC DRUG LABEL
Date: 20220204

ACTIVE INGREDIENTS: ZINC OXIDE 200 mg/1 mL
INACTIVE INGREDIENTS: WATER; COCONUT OIL; BUTYLOCTYL SALICYLATE; DIHEPTYL SUCCINATE; METHYL DIHYDROABIETATE; SHEA BUTTER; CAPRYLOYL GLYCERIN/SEBACIC ACID COPOLYMER (2000 MPA.S); SODIUM STEAROYL GLUTAMATE; CETOSTEARYL ALCOHOL; COCOA BUTTER; HYALURONATE SODIUM; LEVOMENOL; TOCOPHEROL; COCO GLUCOSIDE; MICROCRYSTALLINE CELLULOSE; CARBOXYMETHYLCELLULOSE SODIUM, UNSPECIFIED FORM; CETYL ALCOHOL; ARACHIDYL ALCOHOL; DOCOSANOL; ARACHIDYL GLUCOSIDE; SODIUM GLUCONATE; PHENOXYETHANOL; ETHYLHEXYLGLYCERIN; CITRIC ACID MONOHYDRATE

Baby Bum SPF50 Mineral Sunscreen Lotion

Active Ingredients

Zinc oxide 20%

Purpose

Sunscreen

Uses

- helps prevent sunburn.
- If used as directed with other sun protection measures (see Directions), decreases the risk of skin cancer and early skin aging caused by the sun.

Warnings

For external use only.

Do not use

on damaged or broken skin.

When using this product:

Keep out of eyes. Rinse with water to remove.

Stop use and ask a doctor

if rash occurs.

Keep out of reach of children .

If swallowed, get medical help or contact a Poison Control Center immediately.

Directions

- apply liberally 15 minutes before sun exposure.
- reapply: after 80 minutes of swimming or sweating.
- immediately after towel drying.
- at least every 2 hours.
- children under 6 months of age: ask a doctor.
- Sun Protection Measures. Spending time in the sun increases your risk of skin cancer and early skin aging, To decrease this risk, regularly use a sunscreen with a Broad Spectrum SPF of 15 or higher and other sun protection measures, including:
- limit time in the sun, especially from 10 a.m. - 2 p.m.
- wear long-sleeve shirts, pants, hats, and sunglasses.

Other Information

- protect this product from excessive heat and direct sun.
- keep outer card for complete directions and warnings

Inactive ingredients

water, cocos nucifera (coconut) oil, butyloctyl salicylate, diheptyl succinate, methyl dihydroabietate, butyrospermum parkii (shea butter), capryloyl glycerin/sebacic acid copolymer, sodium stearoyl glutamate, cetearyl alcohol, theobroma cacao (cocoa) seed butter, sodium hyaluronate, bisabolol, tocopherol, coco-glucoside, microcrystalline cellulose, cellulose gum, cetyl alcohol, arachidyl alcohol, behenyl alcohol, arachidyl glucoside, polyhydroxystearic acid, sodium gluconate, phenoxyethanol, ethylhexylglycerin, citric acid

Questions?

call 1 877-978-6286